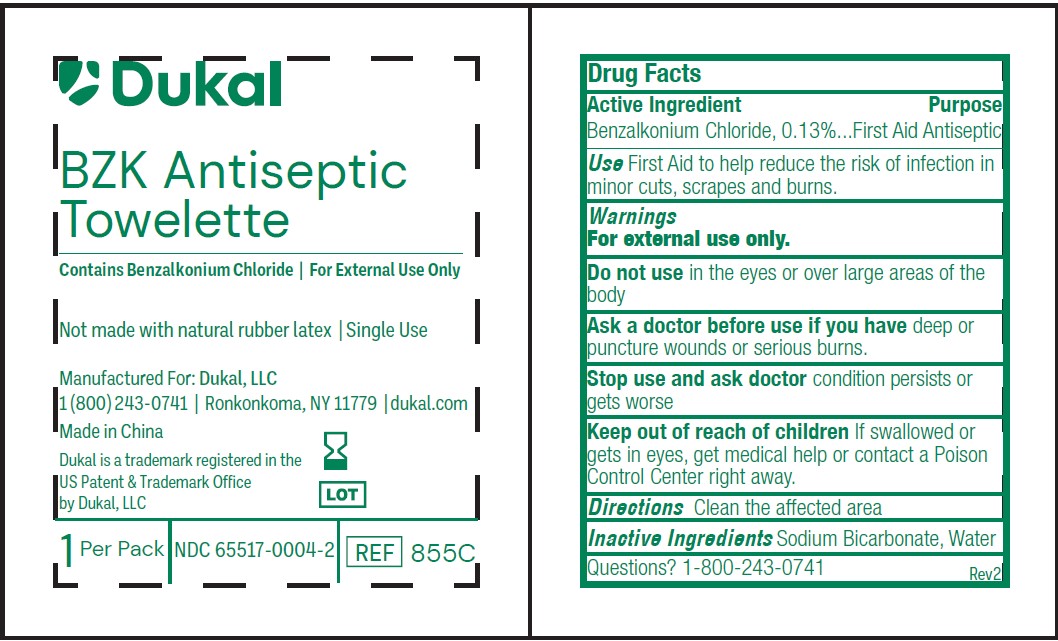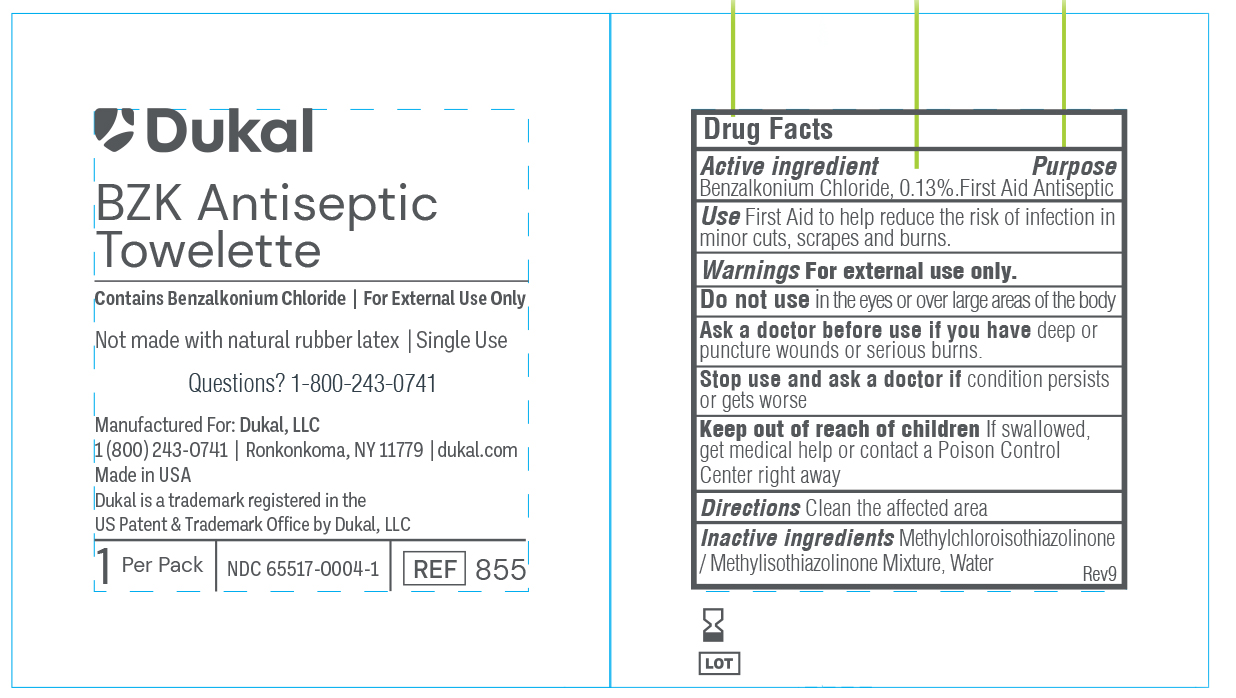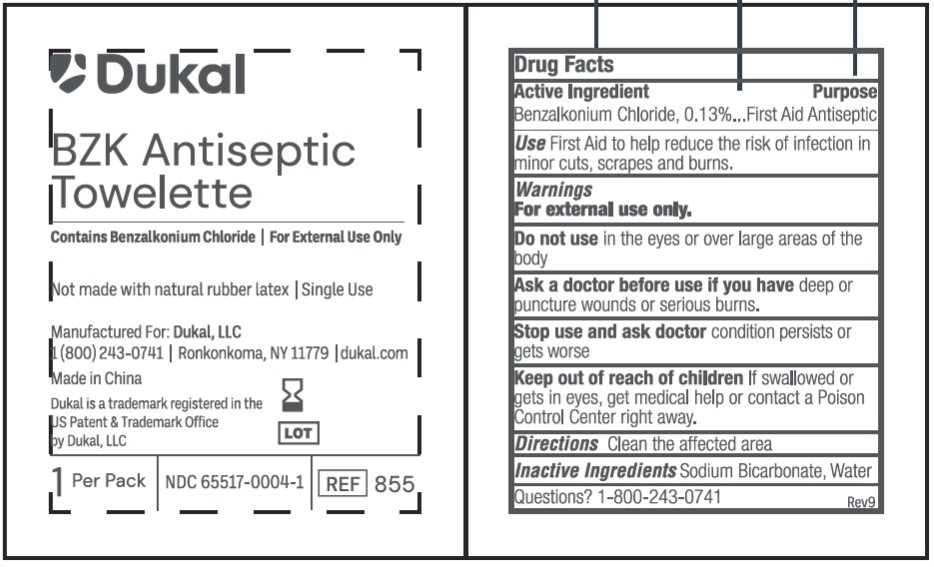 DRUG LABEL: BZK Towelette
NDC: 65517-0004 | Form: SWAB
Manufacturer: Dukal LLC
Category: otc | Type: HUMAN OTC DRUG LABEL
Date: 20250513

ACTIVE INGREDIENTS: BENZALKONIUM CHLORIDE 1.3 mg/1 mL
INACTIVE INGREDIENTS: WATER; SODIUM BICARBONATE; METHYLCHLOROISOTHIAZOLINONE/METHYLISOTHIAZOLINONE MIXTURE

65517-0004 - BZK

Drug Facts

Active Ingredients

Benzalkonium Chloride, 0.133% w/v

Use

First Aid to help reduce the risk of infection in minor cuts, scrapes and burns.

Purpose

First Aid Antiseptic

Do Not Use

In the eyes or apply over large areas of the body.

Stop Use

If irritation, redness or other symptoms develop. Consult a doctor if the condition persists or gets worse.

Caution

Keep out of reach of children.

If swallowed, get medical help or contact a Poison Control Center right away.

Directions

Tear open packet, unfold and use as a washcloth.

Inactive Ingredients

Methylchloroisothiazolinone/Methylisothiazolinone mixture, Sodium Bicarbonate, Water

Principal Display Panel - 1.4 mL Pouch Label

Dukal
BZK ANTISEPTIC

TOWELETTE

Contains Benzalkonium Chloride / For External Use Only

Not made with natural rubber latex / Single Use

Manufactured For: Dukal, LLC

1(800)243-0741 / Ronkonkoma, NY 11779 / dukal.com

Made in USA

Dukal is a trademark registered in the

US Patent & Trademark Office

by Dukal, LLC

1 Per Pack / NDC 65517-0004-1 REF 855

Principal Display Panel - 2.1 mL Pouch Label

Dukal
BZK ANTISEPTIC

TOWELETTE

Contains Benzalkonium Chloride / For External Use Only

Not made with natural rubber latex / Single Use

Manufactured For: Dukal, LLC

1(800)243-0741 / Ronkonkoma, NY 11779 / dukal.com

Made in China

Dukal is a trademark registered in the

US Patent & Trademark Office

by Dukal, LLC

1 Per Pack / NDC 65517-0004-2 / REF 855C

Principal Display Panel - 1.4 mL Pouch Label (China)

Dukal
BZK ANTISEPTIC

TOWELETTE

Contains Benzalkonium Chloride / For External Use Only

Not made with natural rubber latex / Single Use

Manufactured For: Dukal, LLC

1(800)243-0741 / Ronkonkoma, NY 11779 / dukal.com

Made in China

Dukal is a trademark registered in the

US Patent & Trademark Office

by Dukal, LLC

1 Per Pack / NDC 65517-0004-1 REF 855